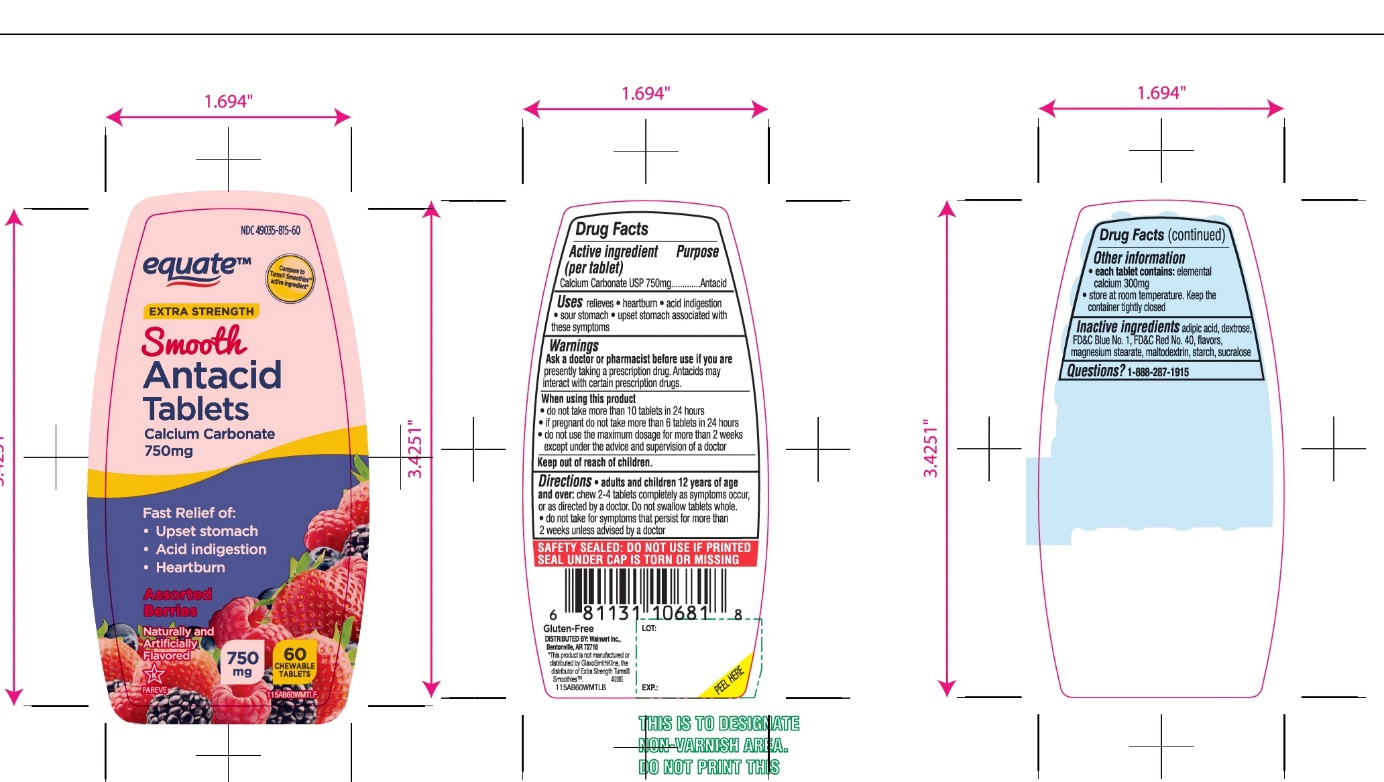 DRUG LABEL: equate Extra Strength Smooth Antacid

NDC: 49035-815 | Form: TABLET, CHEWABLE
Manufacturer: Wal-Mart Stores,Inc.,
Category: otc | Type: HUMAN OTC DRUG LABEL
Date: 20251027

ACTIVE INGREDIENTS: CALCIUM CARBONATE 750 mg/1 1
INACTIVE INGREDIENTS: ADIPIC ACID; FD&C BLUE NO. 1; DEXTROSE, UNSPECIFIED FORM; MAGNESIUM STEARATE; MALTODEXTRIN; FD&C RED NO. 40; STARCH, CORN; SUCRALOSE

equate Extra Strength Smooth Antacid 750 mg Assorted Berries Chewable Tablets

Active ingredient (per tablet)

Calcium Carbonate USP 750mg

Purpose

Antacid

Uses

relieves

- heartburn
- acid indigestion
- sour stomach
- upset stomach associated with these symptoms

Warnings

Ask a doctor or pharmacist before use if you arepresently taking a prescription drug. Antacids may interact with certain prescription drugs.

When using this product

- do not take more than 10 tablets in 24 hours
- if pregnant do not take more than 6 tablets in 24 hours
- do not use the maximum dosage for more than 2 weeks except under the advice and supervision of a doctor

Directions

- adults and children 12 years of age and over:chew 2-4 tablets completely as symptoms occur, or as directed by a doctor. Do not swallow tablets whole.
- do not take for symptoms that persist for more than 2 weeks unless advised by a doctor

Other information

- each tablet contains:elemental calcium 300mg
  Store at room temperature. Keep the container tightly closed

Inactive ingredients

adipic acid, dextrose, FD&C Blue No. 1 , FD&C Red No. 40, flavors, magnesium stearate, maltodextrin, starch, sucralose.

Questions?

1-888-287-1915

SAFETY SEALED: DO NOT USE IF PRINTED SEAL UNDER CAP IS TORN OR MISSING

Package/Label Principal Display Panel

equate™

Compare to Tums® Smoothies™ Active Ingredient*

Extra Strength

Smooth

Antacid Tablets

Calcium Carbonate 750 mg

Fast Relief of;

- Upset
- Acid indigestion
- Heartburn

Assorted Berries

Naturally and Artificially Flavored

K PAREVE

750 mg

60 CHEWABLE TABLETS

GLUTEN- FREE

DISTRIBUTED BY: WalMart Inc.,

Bentonville, AR 72716

*This product is not manufactured or distributed by GlaxoSmithKline, the distributor of Extra Strength TUMS® Smoothies™.